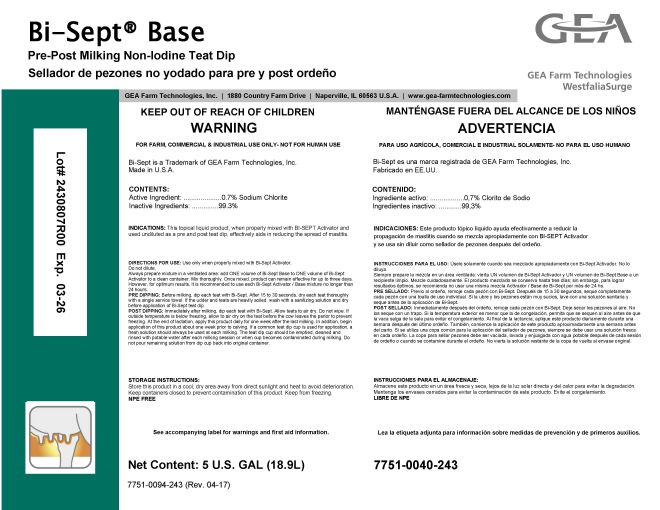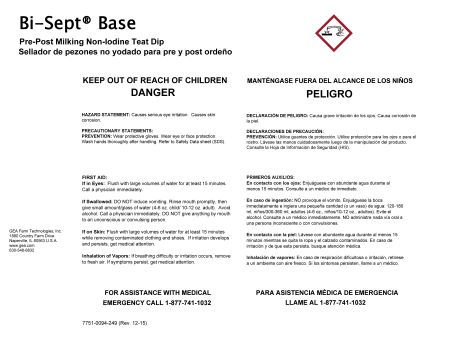 DRUG LABEL: GEA Bi-Sept Base Pre-Post Milking Non-Iodine Teat Dip
NDC: 51070-7015 | Form: LIQUID
Manufacturer: GEA Farm Technologies, Inc.
Category: animal | Type: OTC ANIMAL DRUG LABEL
Date: 20240530

ACTIVE INGREDIENTS: SODIUM CHLORITE 0.7 g/100 g

Bi-Sept Base

ACTIVE INGREDIENT

CONTENTS:

Active Ingredient: 0.7% Sodium Chlorite

INACTIVE INGREDIENTS: 99.3%

Net Content: 5 U.S. GAL (18.9L)

KEEP OUT OF REACH OF CHILDREN

DANGER

PRECAUTIONS

HAZARD STATEMENT:

Causes serious eye irritation. Causes skin corrosion.

PRECAUTIONARY STATEMENTS:

PREVENTION: Wear protective gloves. Wear eye or face protection. Wash hands thoroughly after handling. Refer to Safety Data sheet (SDS).

USER SAFETY WARNINGS

FIRST AID

If in Eyes: Flush with large volumes of water for at least 15 minutes. Call a physician immediately.
If Swallowed: DO NOT induce vomiting. Rinse mouth promptly, then give small amount/glass of water (4-6 oz. child / 10-12 oz. adult). Avoid alcohol. Call a physician immediately. DO NOT give anything by mouth to an unconscious or convulsing person.
If on Skin: Flush with large volumes of water for at least 15 minutes while removing contaminated clothing and shoes. If irritation develops and persists, get medical attention.
Inhalation of Vapors: If breathing difficulty or irritation occurs, remove to fresh air. If symptoms persist, get medical attention.

FOR ASSISTANCE WITH MEDICAL EMERGENCY

CALL 1-877-741-1032.

FOR FARM, COMMERCIAL & INDUSTRIAL USE ONLY

- NOT FOR HUMAN USE

Bi-Sept is a Trademark of GEA Farm Technologies, Inc.

Made in U.S.A.

INDICATIONS AND USAGE

INDICATIONS: This topical liquid product, when properly mixed with Bi-SEPT Activator and used undiluted as a pre and post teat dip, effectively aids in reducing the spread of mastitis.

DOSAGE AND ADMINISTRATION

DIRECTIONS FOR USE: Use only when properly mixed with Bi-Sept Activator. Do not dilute. Always prepare mixture in a ventilated area: add ONE volume of Bi-Sept Base to ONE volume of Bi-Sept Activator to a clean container. Mix thoroughly. Once mixed, product can remain effective for up to three days. However, for optimum results, it is recommended to use each Bi-Sept Activator / Base mixture no longer tha 24 hours.

PRE DIPPING: Before milking, dip each teat with Bi-Sept. After 15 to 30 seconds, dry each treat thoroughly with a single service towel. If the udder and teats are heavily soiled, wash with a sanitizing solution and dry before application of Bi-Spet teat dip.

POST DIPPING: Immediately after milking, dip each teat with Bi-Sept. Allow teats to air dry. Do not wipe. If outside temperature is below freezing, allow to air dry on the teat before the cow leaves the parlor to prevent freezing. At the end of lactation, apply this product daily for one week after the last milking. In addition, begin application of this product about one week prior to calving. If a common teat dip cup is used for application, a fresh solution should always be used at each milking. The teat dip cup should be emptied, cleaned and rinsed with potable water after each milking session or when cup becomes contaminated during milking. Do not pour remaining solution from dip cup back into original container.

STORAGE INSTRUCTIONS:

Store this product in a cool, dry area away from direct sunlight and heat to avoid deterioration. Keep containers closed to prevent contamination of this product. Keep from freezing.

NPE FREE

See accompanying label for warnings and first aid information.

7751-0094-243 (Rev. 04-17)

GEA Farm Technologies, Inc. • 1880 Country Farm Drive • Naperville, IL 60563 U.S.A • www.gea-farmtechnologies.com

7751-0040-243

GEA Farm Technologies, Inc.

1880 Country Farm Dr.

Naperville, IL 60563 U.S.A.

630-548-8832

7751-0094-249 (Rev. 12-15)

PACKAGE LABEL

Bi-Sept® Base

Pre-Post Milking Non-Iodine Teat Dip